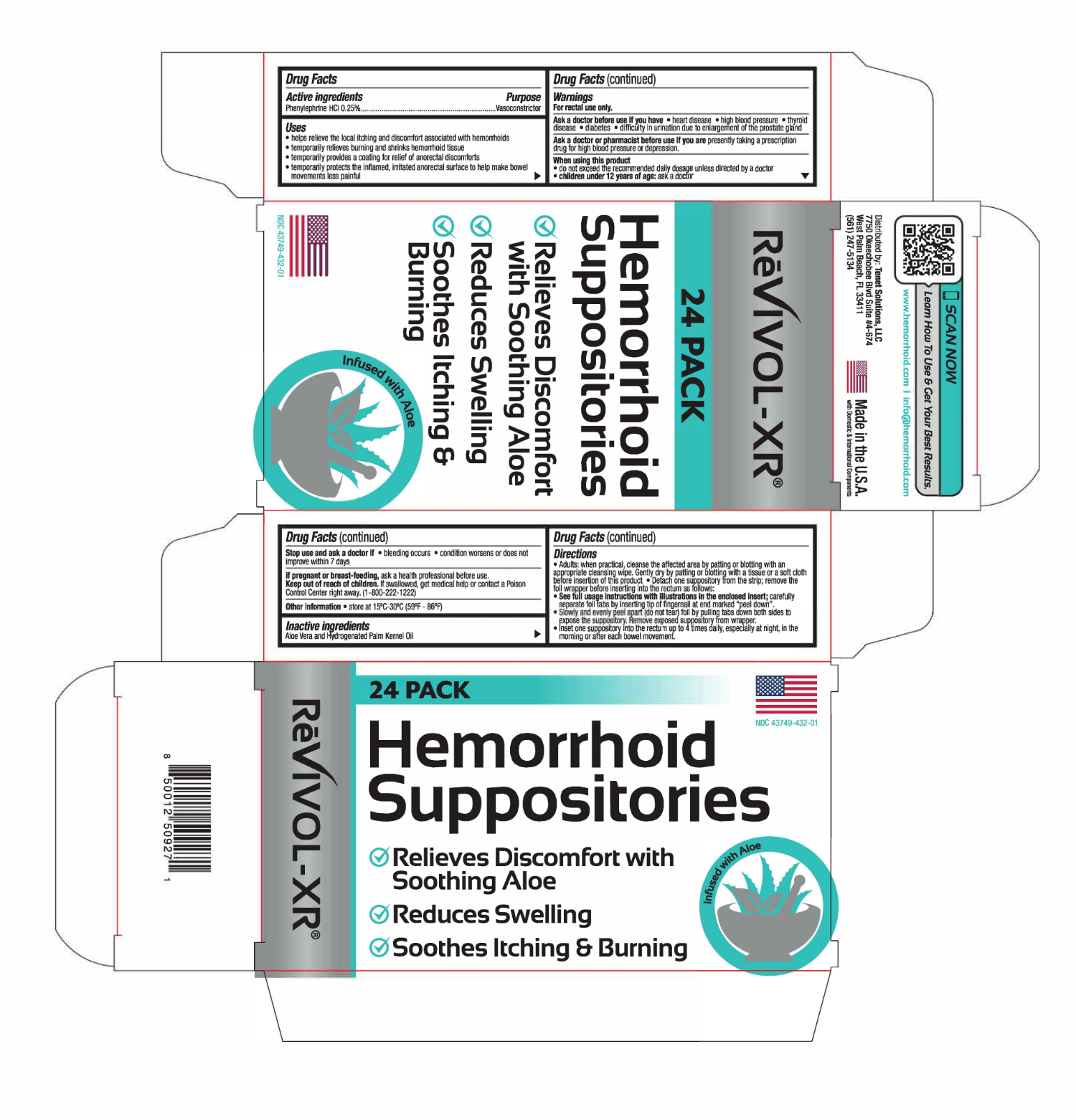 DRUG LABEL: ReVIVOL-XR
NDC: 43749-432 | Form: SUPPOSITORY
Manufacturer: Unipack LLC
Category: otc | Type: HUMAN OTC DRUG LABEL
Date: 20250713

ACTIVE INGREDIENTS: PHENYLEPHRINE HYDROCHLORIDE 6.25 mg/1 1
INACTIVE INGREDIENTS: HYDROGENATED PALM KERNEL OIL; ALOE VERA LEAF

ReVIVOL-XR Hemorrhoid Suppositories

Active Ingredients

Phenylephrine HCl 0.25%

Purposes

Protectant

Vasoconstrictor

Uses

- helps relieve the local itching and discomfort associated with hemorrhoids
- temporarily relieves burning and shrinks hemorrhoidal tissue
- temporarily provides a coating for relief of anorectal discomforts
- temporarily protects the inflamed, irritated anorectal surface to help make bowel movements less painful

Warnings

For rectal use only

Ask a doctor before use if you have

- heart disease
- high blood pressure
- thyroid disease
- diabetes
- difficulty in urination due to enlargement of the prostate gland

ASK DOCTOR/PHARMACIST

presently taking a prescription drug for high blood pressure or depression.

When using this product

- do not exceed the recommended daily dosage unless directed by a doctor
- children under 12 years of age:Ask a doctor

Stop use and ask a doctor if

- bleeding occurs
- condition worsens or does not improve within 7 days

If pregnant or breast-feeding,

ask a health professional before use.

Keep out of reach of children.

If swallowed, get medical help or contact a Poison Control Center right away. (1-800-222-1222)

Directions

- Adults:when practical, cleanse the affected area by patting or blotting with an appropriate cleansing wipe. Gently dry by patting or blotting with a tissue or a soft cloth before insertion of this product.
- Detach one suppository from the strip; remove the foil wrapper before inserting into the rectum as follows:
  - See full usage instructions with illustrations in the enclosed insert; carefully separate foil tabs by inserting tip of fingernail at end marked “peel down”.
  - Slowly and evenly peel apart (do not tear) foil by pulling tabs down both sides, to expose the suppository. Remove the exposed suppository from the wrapper.
  - Insert one suppository into the rectum up to 4 times daily, especially at night, in the morning or after each bowel movement.

Other information

store at 15°C-30°C (59°F-86°F)

Inactive ingredients

Aloe Vera Extract and Hydrogenated Palm Kernel Oil

NDC 43749-432-01

ReVIVOL-XR®

HEMORRHOIDAL SUPPOSITORIES

Reduces Internal Swelling, Soothes and Protects

- Prompt Soothing Relief from Painful Burning, Itching and Discomfort
- Shrinks Swollen Hemorrhoidal Tissue
- Protects Irritated Tissue
- Also for Nighttime Relief

24 SUPPOSITORIES